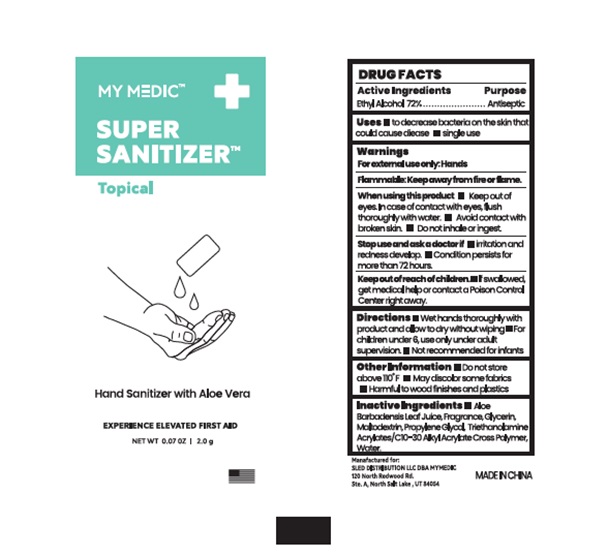 DRUG LABEL: MY MEDIC SUPER SANITIZER
NDC: 81417-008 | Form: GEL
Manufacturer: Sled Distribution, LLC
Category: otc | Type: HUMAN OTC DRUG LABEL
Date: 20240115

ACTIVE INGREDIENTS: ALCOHOL 72 g/100 g
INACTIVE INGREDIENTS: ALOE VERA LEAF; TROLAMINE; PROPYLENE GLYCOL; WATER; GLYCERIN; MALTODEXTRIN; CARBOMER COPOLYMER TYPE A

81417-008 MY MEDIC SUPER SANITIZER

Active Ingredients

Ethyl Alcohol 72%

Purpose

Antiseptic

Uses

- to decrease bacterica on the skin that could cause diease
- single use

Warnings

For external use only: Hands

Flammable: Keep away from fire or flame.

When using this product

- Keep out of eyes. ln case of contact with eyes, flush thoroughly with water.
- Avoid contact with broken skin.
- Do not inhale or ingest.

Stop use and ask a doctor if

- irritation and redness develop.
- Condition persists for more than 72 hours.

Keep out of reach of children.

- If swallowed, get medical help or contact a Poison Control Center right away.

Directions

- Wet hands thoroughly with product and allow to dry without wiping.
- For children under 6, use only under adult supervision.
- Not recommended for infants.

Inactive ingredients

Aloe Barbadensis Leaf Juice, Fragrance, Glycerin, Maltodextrin, Propylene Glycol, Triethanolamine Acrylates/C10-30 Alkyl Acrylate Cross Polymer, Water.